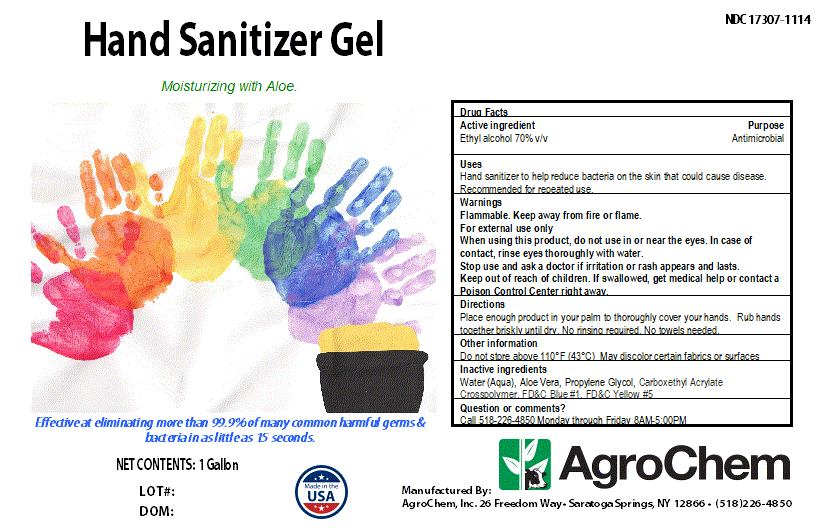 DRUG LABEL: Hand Sanitizer Gel
NDC: 17307-1114 | Form: SOLUTION
Manufacturer: AgroChem inc
Category: otc | Type: HUMAN OTC DRUG LABEL
Date: 20200405

ACTIVE INGREDIENTS: ALCOHOL 0.7 mL/1 mL
INACTIVE INGREDIENTS: PROPYLENE GLYCOL; FD&C YELLOW NO. 5; FD&C BLUE NO. 1; AMMONIUM ACRYLOYLDIMETHYLTAURATE; ALOE VERA LEAF; WATER

Active Ingredient(s)

Ethyl alcohol 70% v/v. Purpose: Antiseptic

Purpose

Antimicrobial

Use

Hand sanitizer to help reduce bacteria on the skin that could cause disease Recommended for repeated use.

Warnings

For external use only. Flammable. Keep away from heat or flame

When using this product keep out of eyes, ears, and mouth. In case of contact with eyes, rinse eyes thoroughly with water.
Stop use and ask a doctor if irritation or rash occurs. These may be signs of a serious condition.
Keep out of reach of children. If swallowed, get medical help or contact a Poison Control Center right away.

Stop use and ask a doctor if irritation or rash occurs. These may be signs of a serious condition.

Keep out of reach of children. If swallowed, get medical help or contact a Poison Control Center right away.

Directions

Place enough product on hands to cover all surfaces. Rub hands together until dry

No rinsing required. No towels needed

Other information

- Do not store above 110°F (43°C) May discolor certain fabrics or surfaces

Inactive ingredients

Water (Aqua), Aloe Vera, Propylene Glycol, Carboxethyl Acrylate Crosspolymer, FD&C Blue #1, FD&C Yellow #5

DESCRIPTION

Hand Sanitizer Gel

Moisturizing with Aloe

Effective at eliminating more than 99.9% of many common harmful germs & bacteria in as little as 15 seconds.

Package Label - Principal Display Panel

3780 mL NDC: 17307-1114-3